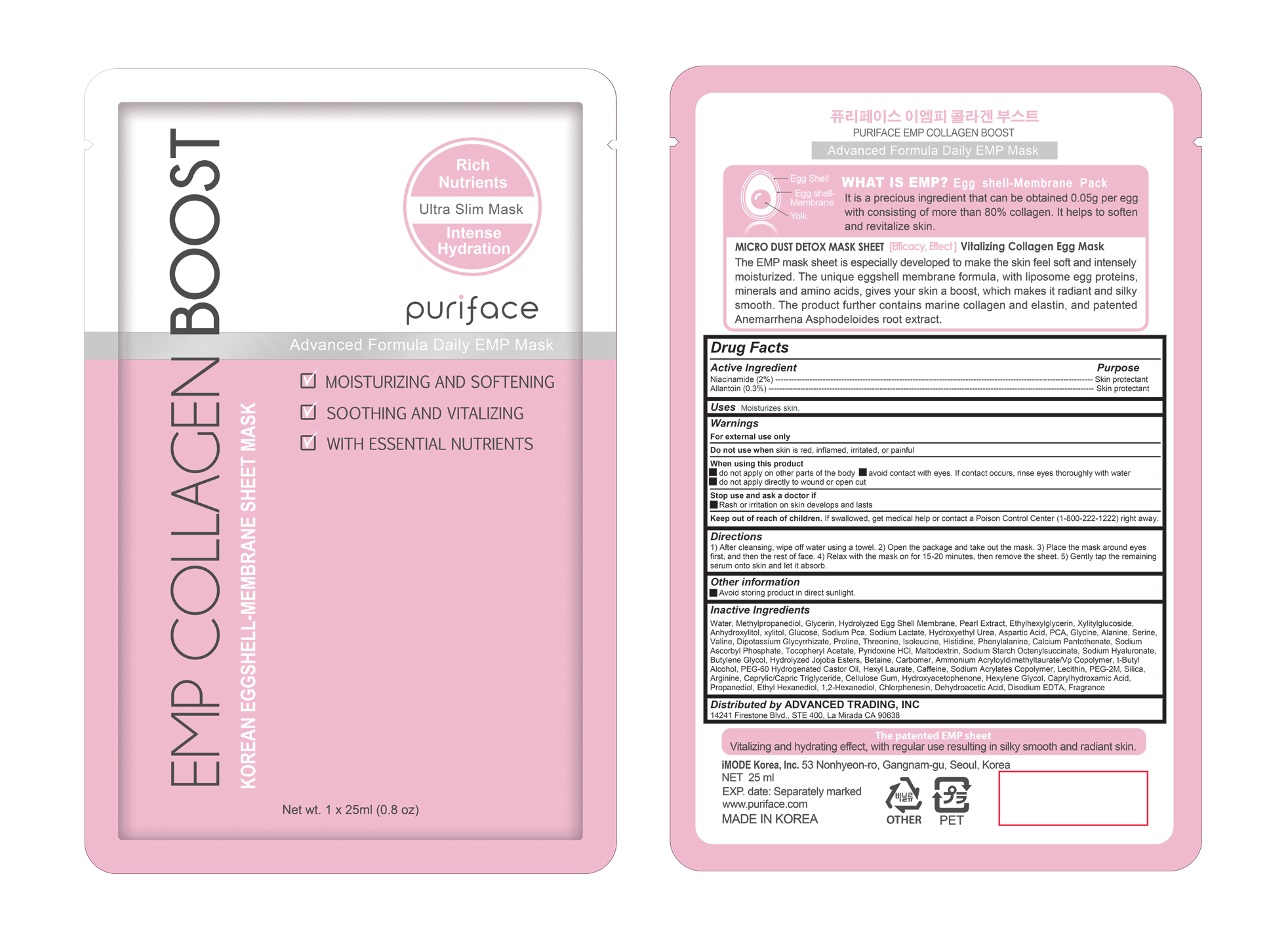 DRUG LABEL: Puripatch for Acne Treatment
NDC: 71727-106 | Form: PATCH
Manufacturer: iMode Korea, Inc.
Category: otc | Type: HUMAN OTC DRUG LABEL
Date: 20200813

ACTIVE INGREDIENTS: SALICYLIC ACID 0.6 g/100 mm
INACTIVE INGREDIENTS: PHENOXYETHANOL; KAOLIN; LIMONENE, (+)-; MELALEUCA ALTERNIFOLIA LEAF; SODIUM HYDROXIDE; LINALOOL, (-)-; WATER; ACRYLIC ACID/DIMETHICONE METHACRYLATE/ETHYLHEXYL ACRYLATE COPOLYMER; EPILOBIUM ANGUSTIFOLIUM WHOLE; SODIUM POLYACRYLATE (8000 MW); C13-14 ISOPARAFFIN; PEG-9 DIGLYCIDYL ETHER/SODIUM HYALURONATE CROSSPOLYMER; NONOXYNOL-30; POLYSORBATE 80; VITIS VINIFERA SEED; LAURETH-7; SODIUM METABISULFITE; PHYTOSPHINGOSINE; ALCOHOL

Puripatch for Acne Treatment

Active ingredients

Niacinamide (2%)

Allantoin (0.3%)

Purpose

Skin protectant

Uses

Moisturizes skin.

Warnings

For external use only

Do not use when skin is red, inflamed, irritated, or painful

When using this product

- do not apply on other parts of the body avoid contact with eyes. If contact occurs, rinse eyes thoroughly with water

- do not apply directly to wound or open cut

Stop use and ask a doctor if

- Rash or irritation on skin develops and lasts

Keep out of reach of children

If swallowed, get medical help or contact a Poison Control Center (1-800-222-1222) right away.

Directions

1) After cleansing, wipe off water using a towel. 2) Open the package and take out the mask. 3) Place the mask around eyes first, and then the rest of face. 4) Relax with the mask on for 15-20 minutes, then remove the sheet. 5) Gently tap the remaining serum onto skin and let it absorb.

Inactive ingredients

Water, Methylpropanediol, Glycerin, Hydrolyzed Egg Shell Membrane, Pearl Extract, Ethylhexylglycerin, Xylitylglucoside, Anhydroxylitol, xylitol, Glucose, Sodium Pca, Sodium Lactate, Hydroxyethyl Urea, Aspartic Acid, PCA, Glycine, Alanine, Serine, Valine, Dipotassium Glycyrrhizate, Proline, Threonine, Isoleucine, Histidine, Phenylalanine, Calcium Pantothenate, Sodium Ascorbyl Phosphate, Tocopheryl Acetate, Pyridoxine HCl, Maltodextrin, Sodium Starch Octenylsuccinate, Sodium Hyaluronate, Butylene Glycol, Hydrolyzed Jojoba Esters, Betaine, Carbomer, Ammonium Acryloyldimethyltaurate/Vp Copolymer, t-Butyl Alcohol, PEG-60 Hydrogenated Castor Oil, Hexyl Laurate, Caffeine, Sodium Acrylates Copolymer, Lecithin, PEG-2M, Silica, Arginine, Caprylic/Capric Triglyceride, Cellulose Gum, Hydroxyacetophenone, Hexylene Glycol, Caprylhydroxamic Acid, Propanediol, Ethyl Hexanediol, 1,2-Hexanediol, Chlorphenesin, Dehydroacetic Acid, Disodium EDTA, Fragrance